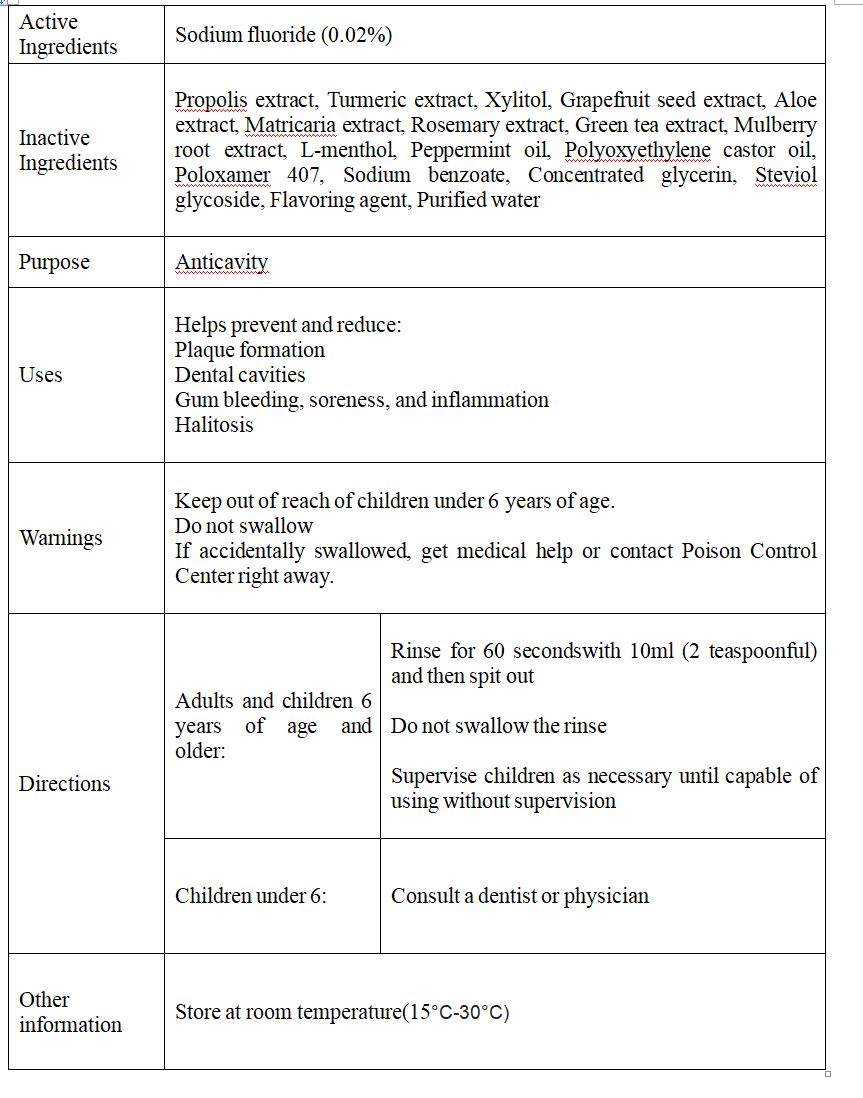 DRUG LABEL: Cool Sense Care Plus Mouthwash
NDC: 76670-0002 | Form: LIQUID
Manufacturer: Dr.s Medi Co.,Ltd.
Category: otc | Type: HUMAN OTC DRUG LABEL
Date: 20210730

ACTIVE INGREDIENTS: SODIUM FLUORIDE 0.02 g/100 mL
INACTIVE INGREDIENTS: WATER

Drug Facts

ACTIVE INGREDIENT

sodium fluoride

INACTIVE INGREDIENT

Propolis extract, Turmeric extract, Xylitol, Grapefruit seed extract, Aloe extract, Matricaria extract, Rosemary extract, Green tea extract, Mulberry root extract, L-menthol, Peppermint oil, Polyoxyethylene castor oil, Poloxamer 407, Sodium benzoate, Concentrated glycerin, Steviol glycoside, Flavoring agent, Purified water

PURPOSE

Helps prevent and reduce:

Plaque formation

Dental cavities

Gum bleeding, soreness, and inflammation

Halitosis

KEEP OUT OF REACH OF THE CHILDREN

INDICATIONS AND USAGE

- Adults and children 6 years of age and older:

Rinse for 60 secondswith 10ml (2 teaspoonful) and then spit out

Do not swallow the rinse

Supervise children as necessary until capable of using without supervision

- Children under 6

Consult a dentist or physician

Keep out of reach of children under 6 years of age.

Do not swallow

If accidentally swallowed, get medical help or contact Poison Control Center right away.

DOSAGE AND ADMINISTRATION

dental use only